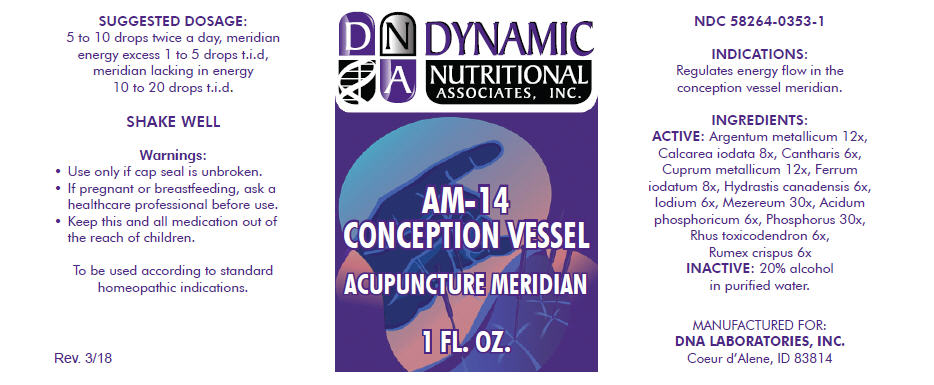 DRUG LABEL: AM-14
NDC: 58264-0353 | Form: SOLUTION
Manufacturer: DNA Labs, Inc.
Category: homeopathic | Type: HUMAN OTC DRUG LABEL
Date: 20250109

ACTIVE INGREDIENTS: SILVER 12 [hp_X]/1 mL; CALCIUM IODIDE 8 [hp_X]/1 mL; LYTTA VESICATORIA 6 [hp_X]/1 mL; COPPER 12 [hp_X]/1 mL; FERROUS IODIDE 8 [hp_X]/1 mL; GOLDENSEAL 6 [hp_X]/1 mL; IODINE 6 [hp_X]/1 mL; DAPHNE MEZEREUM BARK 30 [hp_X]/1 mL; PHOSPHORIC ACID 6 [hp_X]/1 mL; PHOSPHORUS 30 [hp_X]/1 mL; TOXICODENDRON PUBESCENS LEAF 6 [hp_X]/1 mL; RUMEX CRISPUS WHOLE 6 [hp_X]/1 mL
INACTIVE INGREDIENTS: ALCOHOL; WATER

AM-14

NDC 58264-0353-1

INDICATIONS

PURPOSE

Regulates energy flow in the conception vessel meridian.

INGREDIENTS

ACTIVE

Argentum metallicum 12x, Calcarea iodata 8x, Cantharis 6x, Cuprum metallicum 12x, Ferrum iodatum 8x, Hydrastis canadensis 6x, Iodium 6x, Mezereum 30x, Acidum phosphoricum 6x, Phosphorus 30x, Rhus toxicodendron 6x, Rumex crispus 6x

INACTIVE

20% alcohol in purified water.

SUGGESTED DOSAGE

5 to 10 drops twice a day, meridian energy excess 1 to 5 drops t.i.d, meridian lacking in energy 10 to 20 drops t.i.d.

STORAGE AND HANDLING

SHAKE WELL

Warnings

- Use only if cap seal is unbroken.

PREGNANCY OR BREAST FEEDING

- If pregnant or breastfeeding, ask a healthcare professional before use.

KEEP OUT OF REACH OF CHILDREN

- Keep this and all medication out of the reach of children.

To be used according to standard homeopathic indications.

PRINCIPAL DISPLAY PANEL - 1 FL. OZ. Bottle Label

DYNAMIC
NUTRITIONAL
ASSOCIATES, INC.

AM-14
CONCEPTION VESSEL

ACUPUNCTURE MERIDIAN

1 FL. OZ.